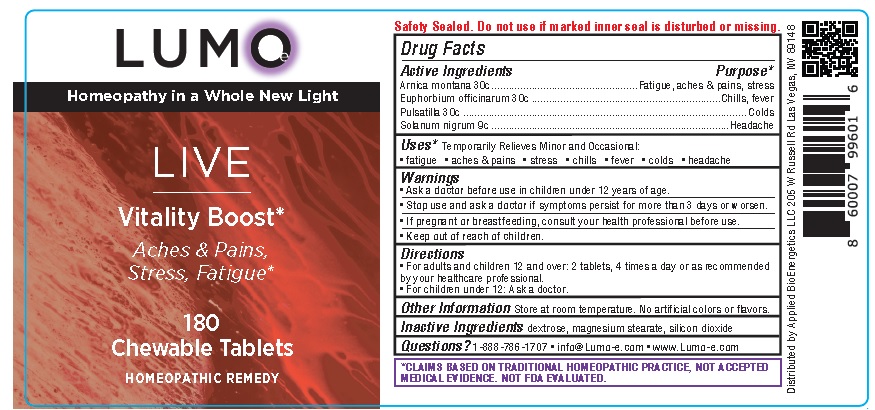 DRUG LABEL: LUMO Live Vitality Boost
NDC: 81425-002 | Form: TABLET, CHEWABLE
Manufacturer: Applied Bioenergetics, LLC
Category: homeopathic | Type: HUMAN OTC DRUG LABEL
Date: 20251110

ACTIVE INGREDIENTS: ARNICA MONTANA 30 [hp_C]/1 1; EUPHORBIA RESINIFERA RESIN 30 [hp_C]/1 1; PULSATILLA PRATENSIS WHOLE 30 [hp_C]/1 1; SOLANUM NIGRUM WHOLE 9 [hp_C]/1 1
INACTIVE INGREDIENTS: DEXTROSE; MAGNESIUM STEARATE; SILICON DIOXIDE

LUMO-e Live Vitality Boost

Drug Facts

Active Ingredients
Arnica montana 30c
Euphorbium officinarum 30c
Pulsatilla 30c
Solanum nigrum 9c

Purpose*
Arnica montana ................................................... Fatigue, aches & pains, stress
Euphorbium officinarum ..................................................................Chills, fever
Pulsatilla ................................................................................................... Colds
Solanum nigrum ..................................................................................Headache

INDICATIONS AND USAGE

Uses* Temporarily Relieves Minor and Occasional:
• fatigue • aches & pains • stress • chills • fever • colds • headache

Warnings
• Ask a doctor before use in children under 12 years of age.
• Stop use and ask a doctor if symptoms persist for more than 7 days or worsen.
• If pregnant or breastfeeding, consult your health professional before use.

• Keep out of reach of children.

Directions
• For adults and children 12 and over: 2 tablets, 4 times a day or as recommended
by your healthcare professional.
• For children under 12: Ask a doctor.

Other Information Store at room temperature. No artificial colors or flavors.

Inactive Ingredients dextrose, magnesium stearate, silicon dioxide

QUESTIONS

Questions? 1-888-786-1707 • info@Lumo-e.com • www.Lumo-e.com

*CLAIMS BASED ON TRADITIONAL HOMEOPATHIC PRACTICE, NOT ACCEPTED
MEDICAL EVIDENCE. NOT FDA EVALUATED.

Product Label for LUMO-e Live Vitality Boost

LUMO-e
Homeopathy in a Whole New Light

Live Vitality Boost

Aches & Pains,
Stress, Fatigue*

180
Chewable Tablets

HOMEOPATHIC REMEDY

Safety Sealed. Do not use if marked inner seal is disturbed or missing.

*CLAIMS BASED ON TRADITIONAL HOMEOPATHIC PRACTICE, NOT ACCEPTED
MEDICAL EVIDENCE. NOT FDA EVALUATED.

Distributed by Applied BioEnergetics LLC 205 W Russell Rd Las Vegas, NV 89148

res